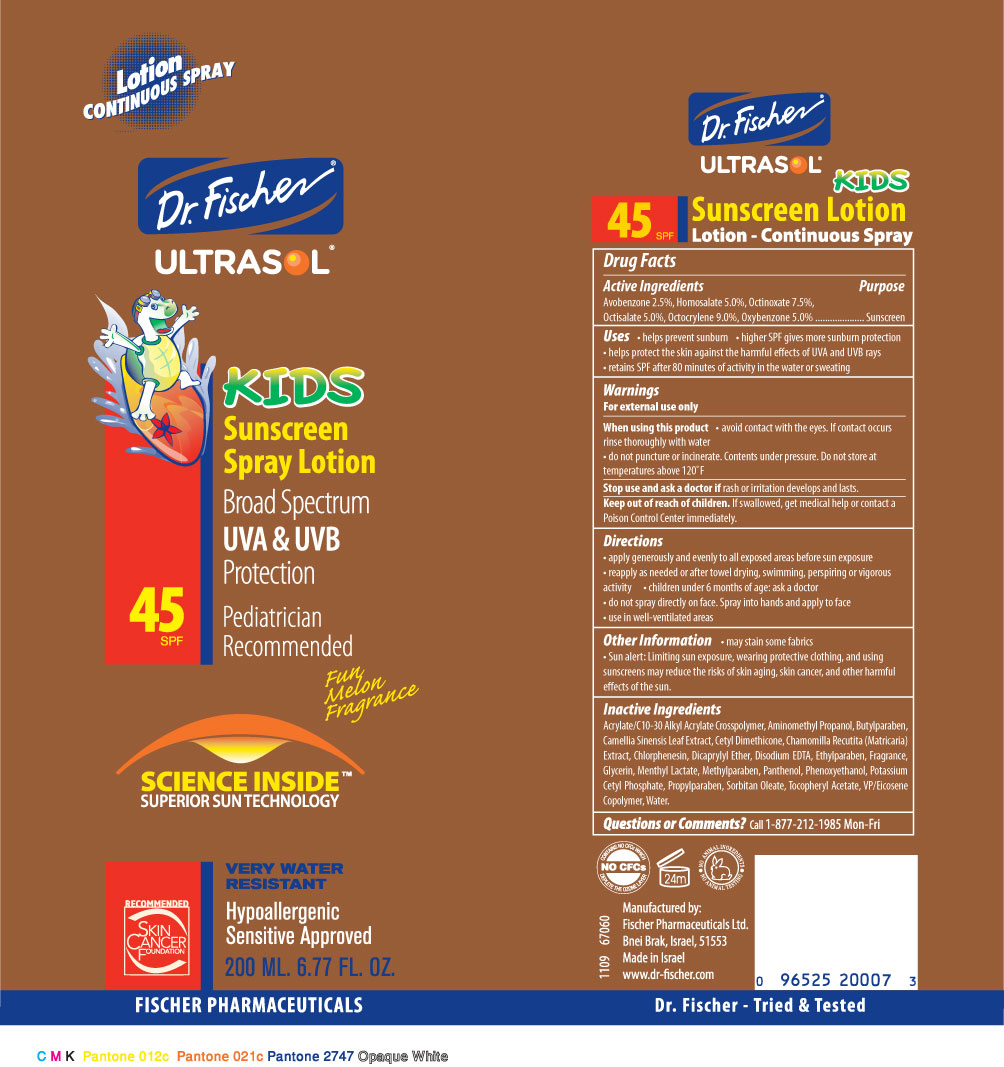 DRUG LABEL: ULTRASOL
NDC: 59886-351 | Form: AEROSOL, SPRAY
Manufacturer: Fischer Pharmaceuticals Ltd
Category: otc | Type: HUMAN OTC DRUG LABEL
Date: 20100506

ACTIVE INGREDIENTS: Avobenzone 2.5 g/100 g; Homosalate 5 g/100 g; Octinoxate 7.5 g/100 g; Octisalate 5 g/100 g; Octocrylene 9 g/100 g; Oxybenzone 5 g/100 g
INACTIVE INGREDIENTS: Butylparaben; Chlorphenesin; EDETATE DISODIUM; Ethylparaben; Glycerin; Methylparaben; Panthenol; Phenoxyethanol; Propylparaben; SORBITAN MONOOLEATE; ALPHA-TOCOPHEROL ACETATE; Water

Dr. Fischer ULTRASOL KIDS Sunscreen Spray Lotion SPF45

Drug Facts

Active Ingredients Purpose
Avobenzone 2.5%, Homosalate 5.0%, Octinoxate 7.5%,
Octisalate 5.0%, Octocrylene 9.0%, Oxybenzone 5.0% .................... Sunscreen

Uses

• helps prevent sunburn • higher SPF gives more sunburn protection
• helps protect the skin against the harmful effects of UVA and UVB rays
• retains SPF after 80 minutes of activity in the water or sweating

Warnings

For external use only

When using this product

• avoid contact with the eyes. If contact occurs
rinse thoroughly with water
• do not puncture or incinerate. Contents under pressure. Do not store at
temperatures above 120°F

Stop use and ask a doctor if

rash or irritation develops and lasts.

Keep out of reach of children.

If swallowed, get medical help or contact a
Poison Control Center immediately.

Directions

• apply generously and evenly to all exposed areas before sun exposure
• reapply as needed or after towel drying, swimming, perspiring or vigorous
activity • children under 6 months of age: ask a doctor
• do not spray directly on face. Spray into hands and apply to face
• use in well-ventilated areas

Other Information

• may stain some fabrics
• Sun alert: Limiting sun exposure, wearing protective clothing, and using
sunscreens may reduce the risks of skin aging, skin cancer, and other harmful
effects of the sun.

Inactive Ingredients

Acrylate/C10-30 Alkyl Acrylate Crosspolymer, Aminomethyl Propanol, Butylparaben,
Camellia Sinensis Leaf Extract, Cetyl Dimethicone, Chamomilla Recutita (Matricaria)
Extract, Chlorphenesin, Dicaprylyl Ether, Disodium EDTA, Ethylparaben, Fragrance,
Glycerin, Menthyl Lactate, Methylparaben, Panthenol, Phenoxyethanol, Potassium
Cetyl Phosphate, Propylparaben, Sorbitan Oleate, Tocopheryl Acetate, VP/Eicosene
Copolymer, Water.

Questions or Comments?

Call 1-877-212-1985 Mon-Fri

PACKAGE LABEL

Dr. Fischer

ULTRASOL

LOTION continuous spray

KIDS Sunscreen Spray Lotion SPF45

Broad Spectrum UVA and UVB Protection

Pediatrician Recommended

Fun Melon Fragrance

SCIENCE INSIDETM SUPERIOR SUN TECHNOLOGY

VERY WATER RESISTANT

Hypoallergenic

Sensitive Approved

RECOMMENDED SKIN CANCER FOUNDATION

200 ML. 6.77 FL. OZ.

FISCHER PHARMACEUTICALS

NO CFCs

Manufactured by:

Fischer Pharmaceuticals Ltd.

Bnei Brak, Israel, 51553

Made in Israel

www.dr-fischer.com

24m

NO ANIMAL INGREDIENTS NO ANIMAL TESTING

Dr. Fischer - Tried and Tested